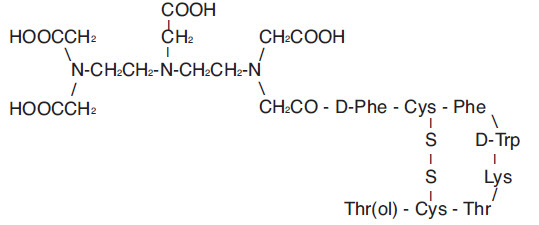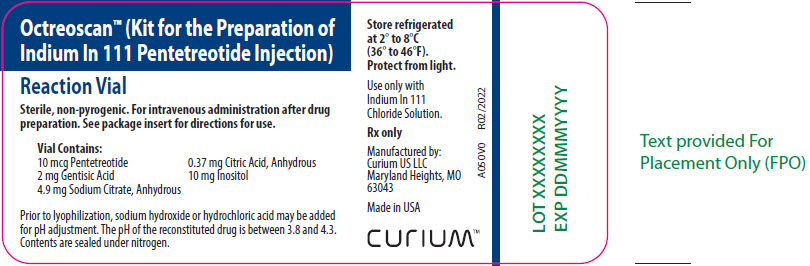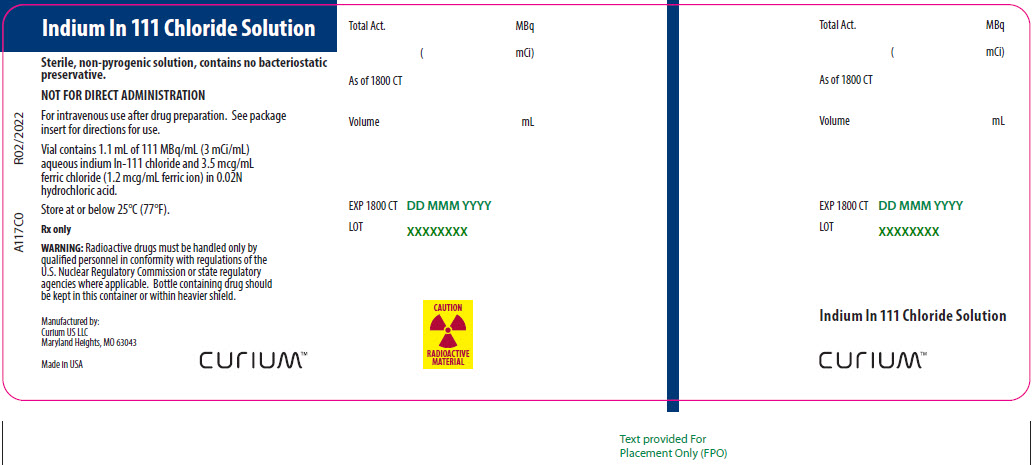 DRUG LABEL: OCTREOSCAN
NDC: 69945-050 | Form: KIT | Route: INTRAVENOUS
Manufacturer: Curium US LLC
Category: prescription | Type: HUMAN PRESCRIPTION DRUG LABEL
Date: 20220221

ACTIVE INGREDIENTS: INDIUM IN-111 PENTETREOTIDE 10 ug/1 mL; INDIUM CHLORIDE IN-111 3 mCi/1 mL
INACTIVE INGREDIENTS: GENTISIC ACID; ANHYDROUS TRISODIUM CITRATE; ANHYDROUS CITRIC ACID; INOSITOL; SODIUM HYDROXIDE; HYDROCHLORIC ACID; HYDROCHLORIC ACID; FERRIC CHLORIDE

OctreoscanTM
(Kit for the Preparation of Indium In 111 Pentetreotide Injection)
Diagnostic - For Intravenous Use.
Rx only

DESCRIPTION

Octreoscan™ is a kit for the preparation of Indium In 111 Pentetreotide Injection, a radioactive diagnostic agent. It is a kit consisting of two components:

1) A 10-mL Octreoscan Reaction Vial which contains a lyophilized mixture of:
(i) 10 mcg pentetreotide [N-(diethylenetriamine-N,N,N′,N″-tetraacetic acid-N″-acetyl)-D-phenylalanyl-L-hemicystyl-L-phenylalanyl-D-tryptophyl-L-lysyl-L-threonyl-L-hemicystyl-L-threoninol cyclic (2→7) disulfide], (also known as octreotide DTPA),
(ii) 2 mg gentisic acid [2, 5-dihydroxybenzoic acid],
(iii) 4.9 mg trisodium citrate, anhydrous,
(iv) 0.37 mg citric acid, anhydrous, and
(v) 10 mg inositol.

Pentetreotide has the following structural formula:

Prior to lyophilization, sodium hydroxide or hydrochloric acid may have been added for pH adjustment. The vial contents are sterile and nonpyrogenic. No bacteriostatic preservative is present.

2) A 10-mL vial of Indium In 111 Chloride Solution, which contains: 1.1 mL or 111 MBq/mL (3 mCi/mL) indium In 111 chloride in 0.02N HCl at time of calibration. The vial also contains ferric chloride at a concentration of 3.5 mcg/mL (ferric ion, 1.2 mcg/mL). The vial contents are sterile and nonpyrogenic. No bacteriostatic preservative is present.

Indium In 111 Pentetreotide Injection is prepared by combining the two kit components (see INSTRUCTIONS FOR THE PREPARATION OF INDIUM In 111 PENTETREOTIDE INJECTION). Indium In-111 reacts with the diethylenetriaminetetraacetic acid portion of the pentetreotide molecule to form indium In 111 pentetreotide. The pH of the resultant Indium In 111 Pentetreotide Injection is between 3.8 and 4.3. No bacteriostatic preservative is present.

The Indium In 111 Pentetreotide Injection is suitable for intravenous administration as is, or it may be diluted to a maximum volume of 3 mL with 0.9% Sodium Chloride Injection, USP, immediately before intravenous administration. In either case, the radiolabeling yield of Indium In 111 Pentetreotide Injection should be determined before administration to the patient. A method recommended for determining the radiolabeling yield is presented at the end of this package insert (see RECOMMENDED METHOD FOR DETERMINATION OF RADIOLABELING YIELD OF INDIUM In 111 PENTETREOTIDE INJECTION).

Physical Characteristics

Indium In-111 decays by electron capture to cadmium-111 (stable) and has a physical half-life of 2.805 days (67.32 hours) (see Table 2). [From Radiopharmaceutical Internal Dosimetry Information Center, Oak Ridge Associated Universities, Oak Ridge, TN 37831-0117, February 1985.] The principal photons that are useful for detection and imaging are listed in Table 1.

Table 1. Principal Radiation Emission Data [Kocher, David C., "Radioactive Decay Data Tables,” DOE/TIC-11026, 115 (1981).]
Radiation | Mean Percent Per Disintegration | Energy (keV)
Gamma-2 | 90.2 | 171.3
Gamma-3 | 94.0 | 245.4

The specific gamma ray constant for In-111 is 3.21 R/hr-mCi at 1 cm. The first half-value thickness of lead (Pb) for In-111 is 0.023 cm. Selected coefficients of attenuation are listed in Table 2 as a function of lead shield thickness. For example, the use of 0.834 cm of lead will attenuate the external radiation by a factor of about 1000.

Table 2. Radiation Attenuation by Lead Shielding
Shield Thickness (Pb) cm | Coefficient of Attenuation
0.023 | 0.5
0.203 | 0.1
0.513 | 0.01
0.834 | 0.001
1.12 | 0.0001

Table 3 lists fractions remaining at selected time intervals before and after calibration. This information may be used to correct for physical decay of the radionuclide.

Table 3. Physical Decay Chart: Indium In-111, Half-life 2.805 Days (67.32 hours)
Hours | Fraction Remaining | Hours | Fraction Remaining
-72 | 2.100 | 0 [Calibration time] | 1.000
-60 | 1.854 | 3 | 0.970
-48 | 1.639 | 6 | 0.940
-36 | 1.448 | 12 | 0.885
-24 | 1.280 | 24 | 0.781
-12 | 1.131 | 36 | 0.690
-6 | 1.064 | 48 | 0.610

CLINICAL PHARMACOLOGY

General

Pentetreotide is a DTPA conjugate of octreotide, which is a long-acting analog of the human hormone, somatostatin. Indium In 111 pentetreotide binds to somatostatin receptors on cell surfaces throughout the body. Within an hour of injection, most of the dose of indium In 111 pentetreotide distributes from plasma to extravascular body tissues and concentrates in tumors containing a high density of somatostatin receptors. After background clearance, visualization of somatostatin receptor-rich tissue is achieved. In addition to somatostatin receptor-rich tumors, the normal pituitary gland, thyroid gland, liver, spleen and urinary bladder also are visualized in most patients, as is the bowel, to a lesser extent. Excretion is almost exclusively via the kidneys.

Pharmacokinetics

Radioactivity leaves the plasma rapidly; one third of the radioactive injected dose remains in the blood pool at 10 minutes after administration. Plasma levels continue to decline so that by 20 hours post-injection, about 1% of the radioactive dose is found in the blood pool. The biological half-life of indium In 111 pentetreotide is 6 hours.

Half of the injected dose is recoverable in urine within 6 hours after injection, 85% is recovered in the first 24 hours, and over 90% is recovered in urine by two days.

Hepatobiliary excretion represents a minor route of elimination, and less than 2% of the injected dose is recovered in feces within three days after injection.

Metabolism

For several hours after administration, plasma radioactivity is predominantly in parent form. Ten percent of the radioactivity excreted is nonpeptide-bound.

Pharmacodynamics

Indium In 111 pentetreotide binds to cell surface receptors for somatostatin. In nonclinical pharmacologic studies, the hormonal effect of Octreoscan in vitro is one-tenth that of octreotide. Since diagnostic imaging doses of indium In 111 pentetreotide are lower than the therapeutic doses of octreotide, indium In 111 pentetreotide is not expected to exert clinically significant somatostatin effects.

Indium In 111 pentetreotide is cleared from the body primarily by renal excretion. Indium In 111 pentetreotide elimination has not been studied in anephric patients or in those with poorly functioning kidneys. It is not known whether indium In 111 pentetreotide can be removed by dialysis. Dosage adjustments in patients with decreased renal function have not been studied.

Clinical Trials

Octreoscan was studied in nine unblinded clinical studies in a total of 365 patients. Of these patients, 174 were male and 191 were female. Their mean age was 54.0 years (range 1.8 to 86 years). One patient was under the age of 2 and 2 patients were between the ages of 2 and 12; 223 patients (61.1%) were between 18 and 60 years; and 136 patients (37.3%) were older than 60 years. A racial distribution is not available.

Eligible patients had a demonstrated or high clinical suspicion of a neuroendocrine tumor. The most common tumors were carcinoids (132 of 309 evaluable patients). Scintigraphic results were compared to results of conventional localization procedures (CT, ultrasound, MRI, angiography, surgery and/or biopsy). The mean dose of radioactivity administered was 173.4 MBq (4.7 mCi).

Octreoscan results were consistent with the final diagnosis (success) in 267 of 309 evaluable patients (86.4%). Compared with carcinoids and gastrinomas, lower success rates were noted for localization of insulinomas, neuroblastomas, pituitary adenomas and medullary thyroid carcinomas. Octreoscan success was observed in 27 of 32 patients (84.4%) with clinically nonfunctioning neuroendocrine tumors (i.e., no symptom of a clinical syndrome mediated by abnormally elevated hormones).

Octreoscan localized previously unidentified tumors in 57/204 patients. In 55/195 patients, indium In 111 pentetreotide uptake occurred in lesions not thought to have somatostatin receptors. In a small subgroup of 39 patients who had tissue confirmation, the sensitivity rate for Octreoscan scintigraphy was 85.7%; for CT/MRI the rate was 68%. The specificity rate for Octreoscan scintigraphy was 50%, the rate for CT/MRI was 12%. Larger studies are needed to confirm these comparisons. Overall, including all tumor types with or without the presence of somatostatin receptors, there were 3/508 false positives and 104/508 false negatives.

Of the 309 patients, 87 had received octreotide for therapeutic purposes within 72 hours of Octreoscan administration. These patients had an overall 95% success rate. The effect of different dose levels of octreotide on success rates has not been evaluated.

INDICATIONS AND USAGE

Octreoscan, after radiolabeling, is an agent for the scintigraphic localization of primary and metastatic neuroendocrine tumors bearing somatostatin receptors.

CONTRAINDICATIONS

None known.

WARNINGS

DO NOT ADMINISTER IN TOTAL PARENTERAL NUTRITION (TPN) ADMIXTURES OR INJECT INTO TPN INTRAVENOUS ADMINISTRATION LINES; IN THESE SOLUTIONS, A COMPLEX GLYCOSYL OCTREOTIDE CONJUGATE MAY FORM.

The sensitivity of scintigraphy with indium In 111 pentetreotide may be reduced in patients concurrently receiving therapeutic doses of octreotide acetate. Consideration should be given to temporarily suspending octreotide acetate therapy before the administration of Indium In 111 Pentetreotide Injection and to monitoring the patient for any signs of withdrawal.

Hypersensitivity reactions following administration of somatostatin receptor imaging agents predominantly consisted of cutaneous reactions such as rash and pruritus. Reactions reversed either spontaneously or with routine symptomatic management. Less frequently hypersensitivity reactions included angioedema or cases with features of anaphylaxis.

PRECAUTIONS

General

1. Therapy with octreotide acetate can produce severe hypoglycemia in patients with insulinomas. Since pentetreotide is an analog of octreotide, an intravenous line is recommended in any patient suspected of having an insulinoma. An intravenous solution containing glucose should be administered just before and during administration of Indium In 111 Pentetreotide Injection.
2. The contents of the two vials supplied with the kit are intended only for use in the preparation of Indium In 111 Pentetreotide Injection and are NOT to be administered separately to the patient.
3. Since indium In 111 pentetreotide is eliminated primarily by renal excretion, use in patients with impaired renal function should be carefully considered.
4. To help reduce the radiation dose to the thyroid, kidneys, bladder, and other target organs, patients should be well hydrated before the administration of Indium In 111 Pentetreotide Injection. They should increase fluid intake and void frequently for one day after administration of this drug. In addition, it is recommended that patients be given a mild laxative (e.g., bisacodyl or lactulose) before and after administration of Indium In 111 Pentetreotide Injection (see DOSAGE AND ADMINISTRATION).
5. Indium In 111 Pentetreotide Injection should be tested for radiolabeling yield of radioactivity prior to administration. The product must be used within 6 hours of preparation.
6. Components of the kit are sterile and nonpyrogenic. To maintain sterility, it is essential that directions are followed carefully. Aseptic technique must be used during the preparation and administration of Indium In 111 Pentetreotide Injection.
7. Octreotide acetate and the natural somatostatin hormone may be associated with cholelithiasis, presumably by altering fat absorption and possibly by decreasing motility of the gallbladder. A single dose of Indium In 111 Pentetreotide Injection is not expected to cause cholelithiasis.
8. As with any other radioactive material, appropriate shielding should be used to avoid unnecessary radiation exposure to the patient, occupational workers, and other persons.
9. Radiopharmaceuticals should be used only by physicians who are qualified by specific training in the safe use and handling of radionuclides.

Carcinogenesis, Mutagenesis, Impairment of Fertility

Studies have not been performed with indium In 111 pentetreotide to evaluate carcinogenic potential or effects on fertility. Pentetreotide was evaluated for mutagenic potential in an in vitro mouse lymphoma forward mutation assay and an in vivo mouse micronucleus assay; evidence of mutagenicity was not found.

Pregnancy

Animal reproduction studies have not been conducted with indium In 111 pentetreotide. It is not known whether indium In 111 pentetreotide can cause fetal harm when administered to a pregnant woman or can affect reproduction capacity. Therefore, Indium In 111 Pentetreotide Injection should not be administered to a pregnant woman unless the potential benefit justifies the potential risk to the fetus.

Nursing Mothers

It is not known whether this drug is excreted in human milk. Because many drugs are excreted in human milk, caution should be exercised when Indium In 111 Pentetreotide Injection is administered to a nursing woman.

Pediatric Use

Safety and effectiveness in pediatric patients have not been established.

ADVERSE REACTIONS

The following adverse effects were observed in clinical trials at a frequency of less than 1% of 538 patients: dizziness, fever, flush, headache, hypotension, changes in liver enzymes, joint pain, nausea, sweating, and weakness. These adverse effects were transient. Also in clinical trials, there was one reported case of bradycardia and one case of decreased hematocrit and hemoglobin.

Pentetreotide is derived from octreotide which is used as a therapeutic agent to control symptoms from certain tumors. The usual dose for Indium In 111 Pentetreotide Injection is approximately 5 to 20 times less than for octreotide and is subtherapeutic. The following adverse reactions have been associated with octreotide in 3% to 10% of patients: nausea, injection site pain, diarrhea, abdominal pain/discomfort, loose stools, and vomiting. Hypertension and hyper- and hypoglycemia have also been reported with the use of octreotide.

The following adverse reactions have been identified during postapproval use of Octreoscan. Because these reactions are reported voluntarily from a population of uncertain size, it is not always possible to reliably estimate their frequency or establish a causal relationship to drug exposure.

Immune System Disorders: Hypersensitivity reactions, predominantly rash, pruritus, less frequently angioedema or features of anaphylaxis.

DOSAGE AND ADMINISTRATION

Before administration, a patient should be well hydrated. After administration, the patient must be encouraged to drink fluids liberally. Elimination of extra fluid intake will help reduce the radiation dose by flushing out unbound, labelled pentetreotide by glomerular filtration. It is also recommended that a mild laxative (e.g., bisacodyl or lactulose) be given to the patient starting the evening before the radioactive drug is administered, and continuing for 48 hours. Ample fluid uptake is necessary during this period as a support both to renal elimination and the bowel-cleansing process. In a patient with an insulinoma, bowel-cleansing should be undertaken only after consultation with an endocrinologist.

The recommended intravenous dose for planar imaging is 111 MBq (3 mCi) of Indium In 111 Pentetreotide Injection prepared from an Octreoscan kit. The recommended intravenous dose for SPECT imaging is 222 MBq (6 mCi) of Indium In 111 Pentetreotide Injection.

The dose should be confirmed by a suitably calibrated radioactivity ionization chamber immediately before administration.

As with all intravenously administered products, Octreoscan should be inspected visually for particulate matter and discoloration prior to administration, whenever solution and container permit. Preparations containing particulate matter or discoloration should not be administered. They should be disposed of in a safe manner, in compliance with applicable regulations.

Aseptic techniques and effective shielding should be employed in withdrawing doses for administration to patients. Waterproof gloves should be worn during the administration procedure.

Do not administer Octreoscan in TPN solutions or through the same intravenous line.

Radiation Dosimetry

The estimated radiation doses [Values listed include a correction for a maximum of 0.1% indium In-114m radiocontaminant at calibration.] to the average adult (70 kg) from intravenous administration of 111 MBq (3 mCi) and 222 MBq (6 mCi) are presented in Table 4. These estimates were calculated by Oak Ridge Associated Universities using the data published by Krenning, et al. [E.P. Krenning, W.H. Bakker, P.P.M. Kooij, W.A.P. Breeman, H.Y. Oei, M. de Jong, J.C. Reubi, T.J. Visser, C. Bruns, D.J. Kwekkeboom, A.E.M. Reijs, P.M. van Hagen, J.W. Koper, and S.W.J. Lamberts, “Somatostatin Receptor Scintigraphy with Indium-111-DTPA-D-Phe-1-Octreotide in Man: Metabolism, Dosimetry and Comparison with Iodine-123-Try-3-Octreotide,” The Journal of Nuclear Medicine, Vol. 33, No. 5, May 1992, pp. 652-658.]

Table 4. Estimated Absorbed Radiation Doses after Intravenous Administration of Indium In 111 Pentetreotide [Assumes 4.8 hour voiding interval and International Commission on Radiological Protection (ICRP) 30 model for the gastrointestinal tract calculations.] to a 70 kg Patient
 | PLANAR |  | SPECT
Organ | mGy/111 MBq | rads/3 mCi | mGy/222 MBq | rads/6 mCi
Kidneys | 54.16 | 5.42 | 108.32 | 10.83
Liver | 12.15 | 1.22 | 24.31 | 2.43
Spleen | 73.86 | 7.39 | 147.73 | 14.77
Uterus | 6.34 | 0.63 | 12.67 | 1.27
Ovaries | 4.89 | 0.49 | 9.79 | 0.98
Testes | 2.90 | 0.29 | 5.80 | 0.58
Red Marrow | 3.46 | 0.35 | 6.91 | 0.69
Urinary Bladder Wall | 30.24 | 3.02 | 60.48 | 6.05
GI Tract
Stomach Wall | 5.67 | 0.57 | 11.34 | 1.13
Small Intestine | 4.78 | 0.48 | 9.56 | 0.96
Upper Large Intestine | 5.80 | 0.58 | 11.59 | 1.16
Lower Large Intestine | 7.73 | 0.77 | 15.46 | 1.55
Adrenals | 7.55 | 0.76 | 15.11 | 1.51
Thyroid | 7.43 | 0.74 | 14.86 | 1.49
 | mSv/111 MBq | rem/3 mCi | mSv/222 MBq | rem/6 mCi
Effective Dose [Estimated according to ICRP Publication 53.] Equivalent | 13.03 | 1.30 | 26.06 | 2.61

HOW SUPPLIED

The Octreoscan kit (NDC 69945-050-40) is supplied with the following components:

1. A 10-mL Octreoscan Reaction Vial which contains a lyophilized mixture of:
  (i) 10 mcg pentetreotide [N-(diethylenetriamine-N,N,N',N”-tetraacetic acid-N”-acetyl)-D-phenylalanyl-L-hemicystyl-L-phenylalanyl-D-tryptophyl-L-lysyl-L-threonyl-L-hemicystyl-L-threoninol cyclic (2→7) disulfide], (also known as octreotide DTPA),
  (ii) 2 mg gentisic acid [2, 5-dihydroxybenzoic acid],
  (iii) 4.9 mg trisodium citrate, anhydrous,
  (iv) 0.37 mg citric acid, anhydrous, and
  (v) 10 mg inositol.
  Before lyophilization, sodium hydroxide or hydrochloric acid may have been added for pH adjustment. The vial contents are sterile and nonpyrogenic. No bacteriostatic preservative is present.
2. A 10-mL vial of Indium In 111 Chloride Solution, which contains 1.1 mL or 111 MBq/mL (3 mCi/mL) Indium In 111 chloride in 0.02 N HCl at time of calibration. The vial also contains ferric chloride at a concentration of 3.5 mcg/mL (ferric ion, 1.2 mcg/mL). The vial contents are sterile and nonpyrogenic. No bacteriostatic preservative is present.

In addition, the kit also contains the following items: (1) a 25 G x 5/8” needle (B-D, Monoject) used to transfer Indium In 111 Chloride Solution to the Octreoscan Reaction Vial, (2) pressure sensitive label, and (3) a package insert.

Storage

The Octreoscan kit should be stored refrigerated at 2° to 8°C (36° to 46°F).

After reconstitution, store at controlled room temperature 20° to 25°C (68° to 77°F). Indium In 111 Pentetreotide Injection must be used within 6 hours of preparation.

INSTRUCTIONS FOR THE PREPARATION OF INDIUM In 111 PENTETREOTIDE INJECTION

Note: Read complete directions thoroughly before starting preparation.

Procedure Precautions and Notes

1. All transfers and penetrations of the vial stoppers by a needle must use aseptic technique.
2. Wear waterproof gloves during the entire procedure and while withdrawing the patient-dose from the Octreoscan Reaction Vial.
3. Transfer Indium In 111 Chloride Solution with an adequately shielded, sterile syringe using the transfer needle in the kit.
4. Adequate shielding should be maintained at all times until the preparation is administered to the patient, disposed of in an approved manner, or allowed to decay to safe levels of radioactivity. A shielded, sterile syringe should be used for withdrawing and injecting the preparation.
5. Do not inject into TPN administration bags or their intravenous lines.

Procedure for the Preparation of Indium In 111 Pentetreotide Injection

1. Place the Octreoscan Reaction Vial in a lead dispensing shield (of minimum wall thickness 1/4 inch) fitted with a lid.
2. Swab the rubber stopper of the reaction vial with an appropriate antiseptic and allow the vial to dry.
3. Aseptically remove the contents of the Indium In 111 Chloride Solution vial using the needle provided and a shielded, sterile syringe.
4. Inject the Indium In 111 Chloride Solution into the Octreoscan Reaction Vial.
5. Gently swirl the Octreoscan Reaction Vial until the lyophilized pellet is completely dissolved.
6. Incubate the Indium In 111 Pentetreotide Injection at or below 25°C (77°F) for a minimum of 30 minutes. Note: A 30 minute incubation time is required. Shorter incubation periods may result in inadequate radiolabeling.
7. Using proper shielding, visually inspect the vial contents. The solution should be clear, colorless, and free of particulate matter. If not, the solution should not be used. It should be disposed in a safe and approved manner.
8. Assay the Indium In 111 Pentetreotide Injection using a suitably calibrated ionization chamber. Record the date, time, total activity, and patient identifier (e.g., patient name and number) on the radioassay information label and affix the label to the lead dispensing shield.
9. The radiolabeling yield of the reconstituted solution should be checked before administration to the patient, according to the instructions given below. If the radiochemical purity is less than 90%, the product should not be used.
10. Store the reaction vial containing the Indium In 111 Pentetreotide Injection at controlled room temperature 20° to 25°C (68° to 77°F) until use. The Indium In 111 Pentetreotide Injection must be used within 6 hours of preparation.
11. If desired, the preparation can be diluted to a maximum volume of 3 mL with 0.9% Sodium Chloride Injection, USP immediately prior to injection. The sample should be drawn up into a shielded, sterile syringe and administered to the patient.

RECOMMENDED METHOD FOR DETERMINATION OF RADIOLABELING YIELD OF INDIUM In 111 PENTETREOTIDE INJECTION

Required Materials

1. Waters Sep-Pak™ C18 Cartridge, Part No. 51910
2. Methanol, 15 mL (Caution: toxic and flammable. Exercise due caution.)
3. Distilled water, 20 mL
4. Disposable syringes:
  2 - 10-mL, no needle required
  2 - 5-mL, no needle required
  1 - 1-mL, with needle
5. Three disposable culture tubes or vials, minimum 10-mL capacity
6. Ion chamber

Preparation of the Sep-Pak Cartridge

1. Rinse the Sep-Pak cartridge with 10 mL methanol as follows: fill a 10-mL syringe with 10 mL methanol, attach the syringe to the longer end of the Sep-Pak cartridge, and push the methanol through the cartridge. Discard the eluate in a safe and approved manner.
2. Similarly, rinse the cartridge with 10 mL water. Ensure that the cartridge is kept wet and that there is no air bubble present. If an air bubble is present, rinse the cartridge with additional 5 mL of water. Discard the eluate.

Sample Analysis

1. Using a 1-mL syringe with needle, withdraw 0.05 to 0.1 mL Indium In 111 Pentetreotide Injection from the Octreoscan Reaction Vial. Apply the preparation to the Sep-Pak cartridge through the longer end of the cartridge. Make sure that the sample is migrating onto the column of the cartridge. Note: After this step, the cartridge and all solutions eluted from it will be radioactive.
2. With a disposable 5-mL syringe, slowly (in dropwise manner) push 5 mL water through the longer end of the cartridge, collecting the eluate in a counting vial or tube. Label this eluate as “Fraction 1.”
3. Similarly, elute the cartridge with 5 mL methanol. Be sure that this solution is pushed slowly through the longer end of the cartridge so that the elution occurs in a dropwise manner. Collect this fraction in a second culture tube or vial for counting. Label it as “Fraction 2.” Push two 5-mL portions of air through the longer end of the cartridge and collect the eluate with Fraction 2.
4. Place the Sep-Pak cartridge in a third culture tube or vial for assay.

Assay

1. Assay the activity of Fraction 1 in a suitably calibrated ionization chamber. This fraction contains the hydrophilic impurities (e.g., unbound indium In-111).
2. Assay the activity of Fraction 2. This fraction contains the indium In 111 pentetreotide.
3. Assay the activity of the Sep-Pak cartridge. This component contains the remaining non-elutable impurities.
4. Dispose of all of the materials used in the preparation, the sample analysis, and the assay in a safe and approved manner.

Calculations

1. Percent Indium In 111 Pentetreotide =
  (Fraction 2 Activity / Total Activity) x 100%
  Where Total Activity = Fraction 1 + Fraction 2 + activity remaining in Sep-Pak
  Note: If this value is less than 90%, do not use the preparation. Discard it in a safe and approved manner.
2. Percent hydrophilic impurities =
  (Fraction 1 Activity / Total Activity) x 100%
3. Percent non-elutable impurities =
  (Activity remaining in Sep-Pak cartridge / Total Activity) x 100%

This radiopharmaceutical is licensed by the Illinois Department of Nuclear Safety for distribution to persons licensed pursuant to 330.260(a) for the radioactive material specified in 32 IL. Adm. Code 335.4010 or under equivalent licenses of the U.S. Nuclear Regulatory Commission, an Agreement State, or a Licensing State.

CuriumTM and the Curium logo are trademarks of a Curium company.
©2022 Curium US LLC. All Rights Reserved.

Sep-PakTM is a trademark of Waters Technologies Corporation.

Manufactured by:
Curium US LLC
Maryland Heights, MO 63043

Made in USA

A050I0

Revised 2/2022 CURIUM™

PRINCIPAL DISPLAY PANEL - A050V0

Octreoscan™ (Kit for the Preparation of Indium In 111 Pentetreotide Injection)

Reaction Vial
Sterile, non-pyrogenic. For intravenous administration after drug preparation. See package insert for directions for use.
Vial Contains:
10 mcg Pentetreotide
2 mg Gentisic Acid
4.9 mg Sodium Citrate, Anhydrous
0.37 mg Citric Acid, Anhydrous
10 mg Inositol
Prior to lyophilization, sodium hydroxide or hydrochloric acid may be added for pH adjustment. The pH of the reconstituted drug is between 3.8 and 4.3. Contents are sealed under nitrogen.

Store refrigerated at 2° to 8°C (36° to 46°F). Protect from light.

Use only with Indium In 111 Chloride Solution.

Rx only

Manufactured by:
Curium US LLC
Maryland Heights, MO 63043

Made in USA
CURIUM™
A050V0

R02/2022

LOT XXXXXXXX

EXP DDMMMYYYY

PRINCIPAL DISPLAY PANEL - A117C0

Indium In 111 Chloride Solution
Sterile, non-pyrogenic solution, contains no bacteriostatic preservative.
NOT FOR DIRECT ADMINISTRATION
For intravenous use after drug preparation. See package insert for directions for use.
Vial contains 1.1 mL of 111 MBq/mL (3 mCi/mL) aqueous indium In-111 chloride and 3.5 mcg/mL ferric chloride (1.2 mcg/mL ferric ion) in 0.02N hydrochloric acid.
Store at or below 25°C (77°F).
Rx only
WARNING: Radioactive drugs must be handled only by qualified personnel in conformity with regulations of the U.S. Nuclear Regulatory Commission or state regulatory agencies where applicable. Bottle containing drug should be kept in this container or within heavier shield.
Manufactured by:
Curium US LLC
Maryland Heights, MO 63043

Made in USA
CURIUM™
CAUTION RADIOACTIVE MATERIAL
A117C0

R02/2022

Total Act. MBq

(mCi)

As of 1800 CT

Volume mL

EXP 1800 CT DD MMM YYYY

LOT XXXXXXXX